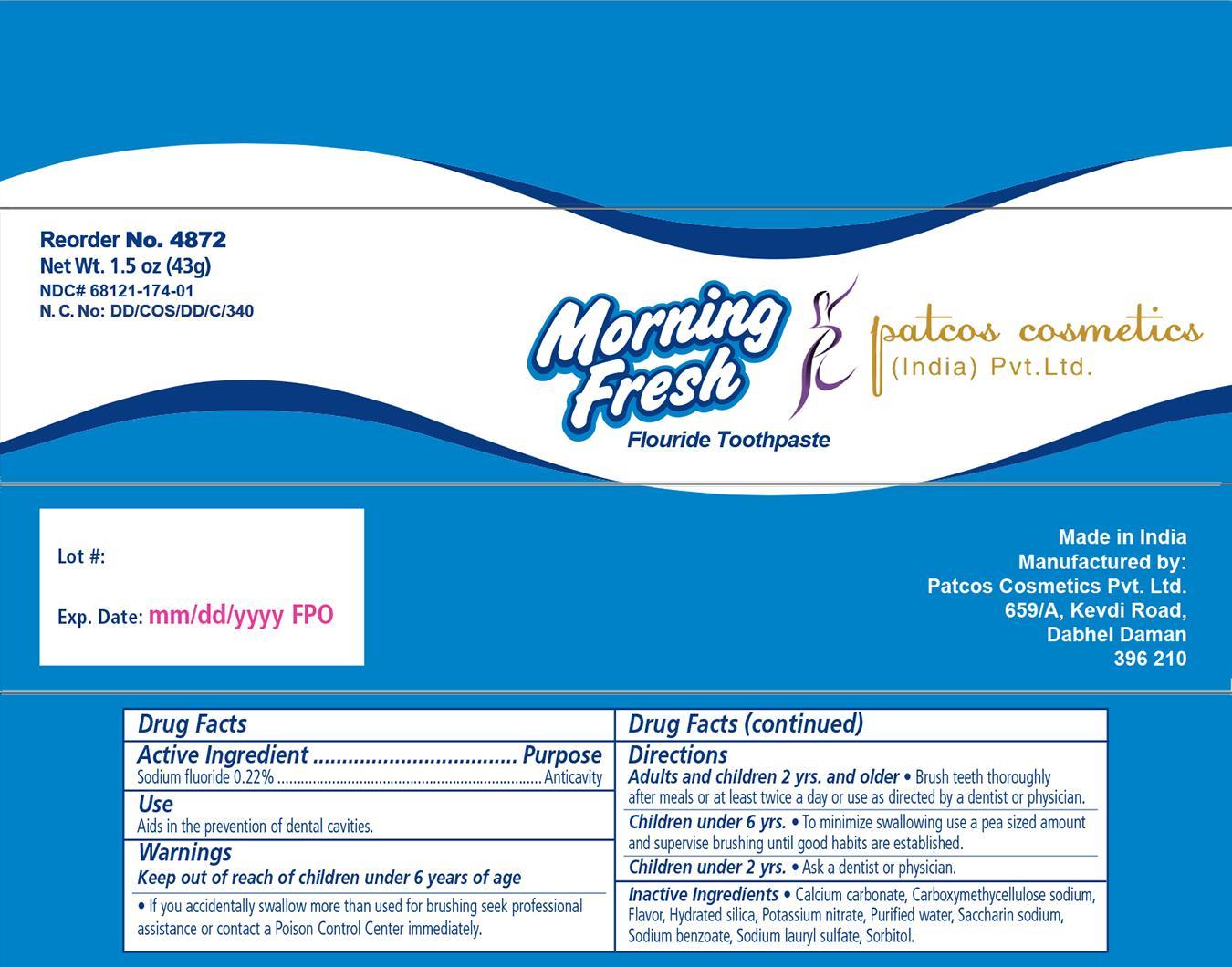 DRUG LABEL: Morning Fresh
NDC: 68121-174 | Form: PASTE
Manufacturer: Patcos Cosmetics (India) Private Limited
Category: otc | Type: HUMAN OTC DRUG LABEL
Date: 20171215

ACTIVE INGREDIENTS: SODIUM FLUORIDE 2.2 mg/1 g
INACTIVE INGREDIENTS: SORBITOL; HYDRATED SILICA; CALCIUM CARBONATE; SODIUM BENZOATE; SACCHARIN SODIUM; WATER; CARBOXYMETHYLCELLULOSE SODIUM; SODIUM LAURYL SULFATE; POTASSIUM NITRATE

Toothpaste

Active Ingredient

Sodium Fluoride 0.22 %

Purpose: Anticavity

Use

- Aids in the prevention of dental cavities.

Inactive Ingredient

Calcium carbonate, Carboxymethycellulose sodium, Flavour, Hydrated silica,Potassium nitrate, Purified water, Saccharin sodium, Sodium benzoate, Sodium lauryl sulfate, Sorbitol

Dosage and Administration

Directions:

- Adults and children 2 years and older Brush teeth thoroughly after meals or at least twice a day or use as directed by a dentist or physician.
- Children under 6 years To minimize swallowing, use a pea sized amount and supervise brushing until good habits are established.
- Children under 2 years Ask a dentist or physician.

Indications and Usage

- The prevention of dental cavities.

Warnings

- If you accidentally swallow more than used for brushing, seek professional assistance or contact a Poison Control Center immediately.

Keep out of reach of children under 6 years of age.

Principal Display Panel

Patcos Toothpaste

Patcos Toothpaste 1.jpg